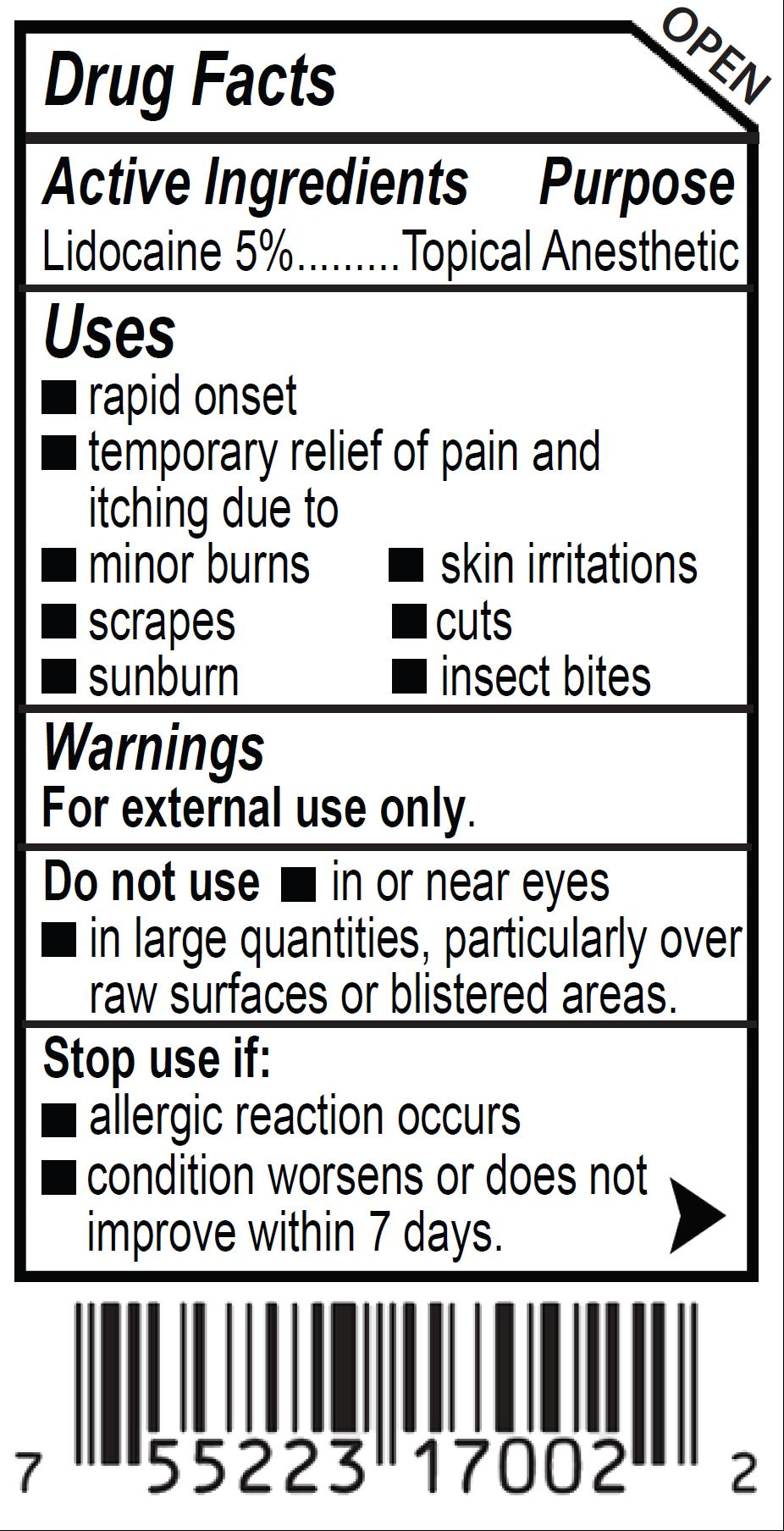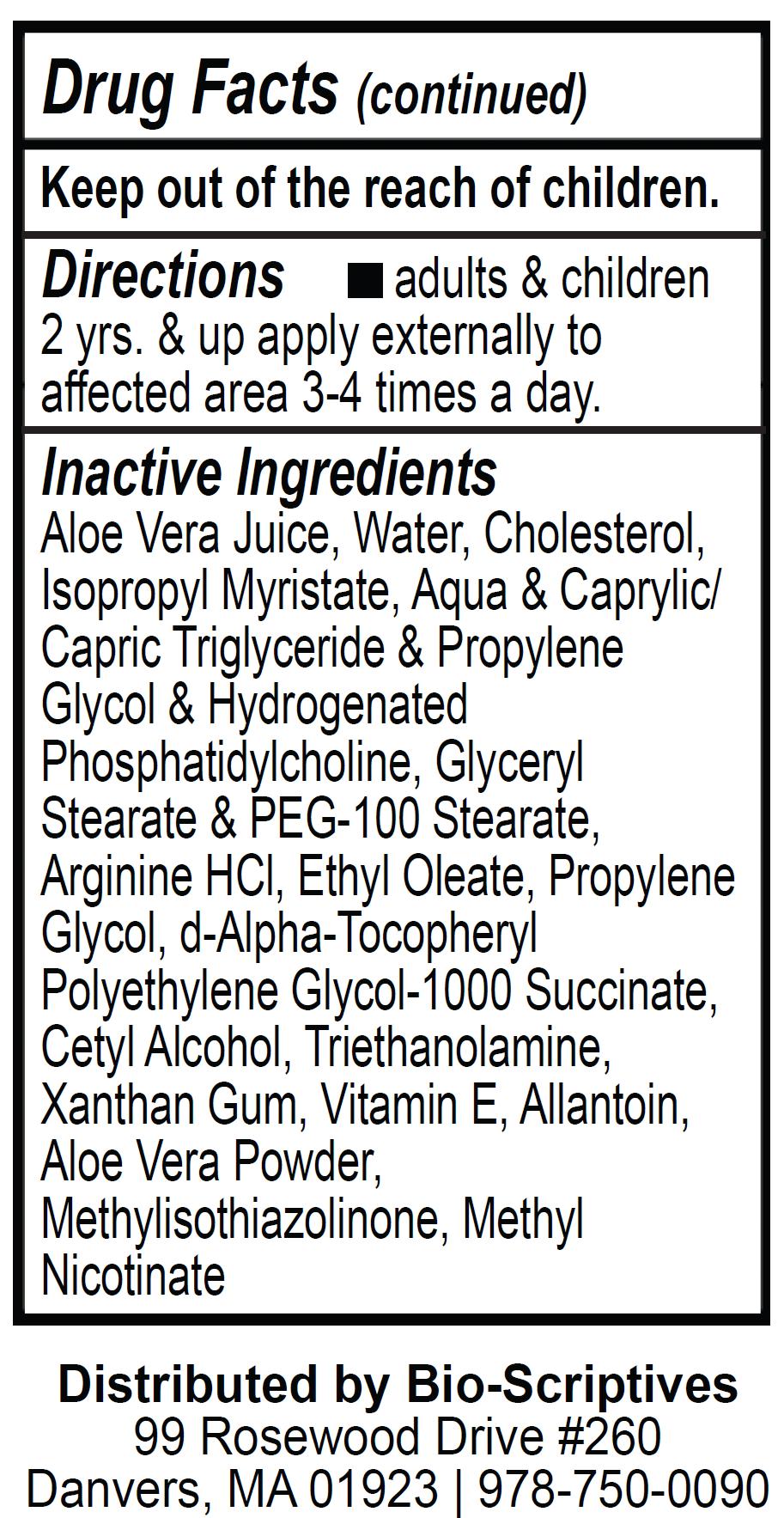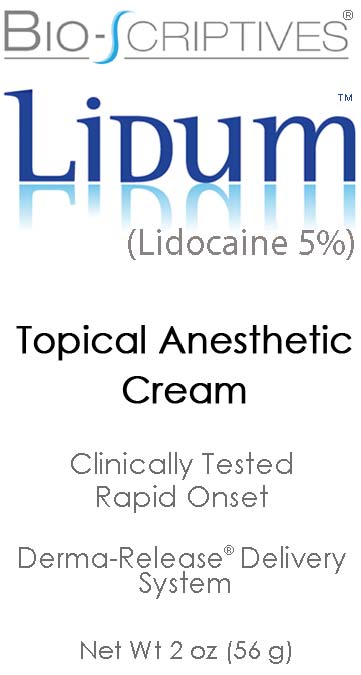 DRUG LABEL: Bio-Scriptives Lidum
NDC: 60608-011 | Form: CREAM
Manufacturer: BioChemics, Inc
Category: otc | Type: HUMAN OTC DRUG LABEL
Date: 20110603

ACTIVE INGREDIENTS: Lidocaine Hydrochloride 2.8 g/56 g
INACTIVE INGREDIENTS: ALOE VERA LEAF; WATER; CHOLESTEROL; ISOPROPYL MYRISTATE; CAPRYLIC/CAPRIC MONO/DIGLYCERIDES; GLYCERYL MONOSTEARATE; ARGININE HYDROCHLORIDE; PROPYLENE GLYCOL; ETHYL OLEATE; TOCOPHERSOLAN; CETYL ALCOHOL; XANTHAN GUM; TROLAMINE; ALLANTOIN; ALPHA-TOCOPHEROL; METHYLISOTHIAZOLINONE; METHYL NICOTINATE; LECITHIN, SOYBEAN; MEDIUM-CHAIN TRIGLYCERIDES; PROPYLENE GLYCOL

Drug Facts

Active Ingredient

Lidocaine 5%

Purpose

Topical Anesthetic

Uses

■ rapid onset
■ temporary relief of pain and itching due to
■ minor burns
■ skin irritations
■ scrapes
■ cuts
■ sunburn
■ insect bites

Warnings

For external use only.

Do Not Use

■ in or near eyes
■ in large quantities, particularly over raw surfaces or blistered areas

Stop use if

■ allergic reaction occurs
■ condition worses or does not improve within 7 days

Keep out of the reach of children.

Directions

■ adults and children 2 years and up apply externally to affected areas 3-4 times a day.

Inactive Ingredients

Aloe Vera Juice, Water, Cholesterol, lsopropyl Myristate, Aqua and Caprylic Capric Triglyceride and Propylene Glycol and Hydrogenated Phosphatitylcholine, Glyceryl Stearate and PEG-100 Stearate, Arginine HCI, Ethyl OLeate, Propylene Glycol, dAlpha-Tocopheryl Polyethylene Glycol-1000 Succinate, Cetyl Alcohol, Triethanolamine, Xanthan Gum, Vitamin E, Allantoin, Aloe Vera Powder, Methylisothiazolinone, Methyl Nicotinate